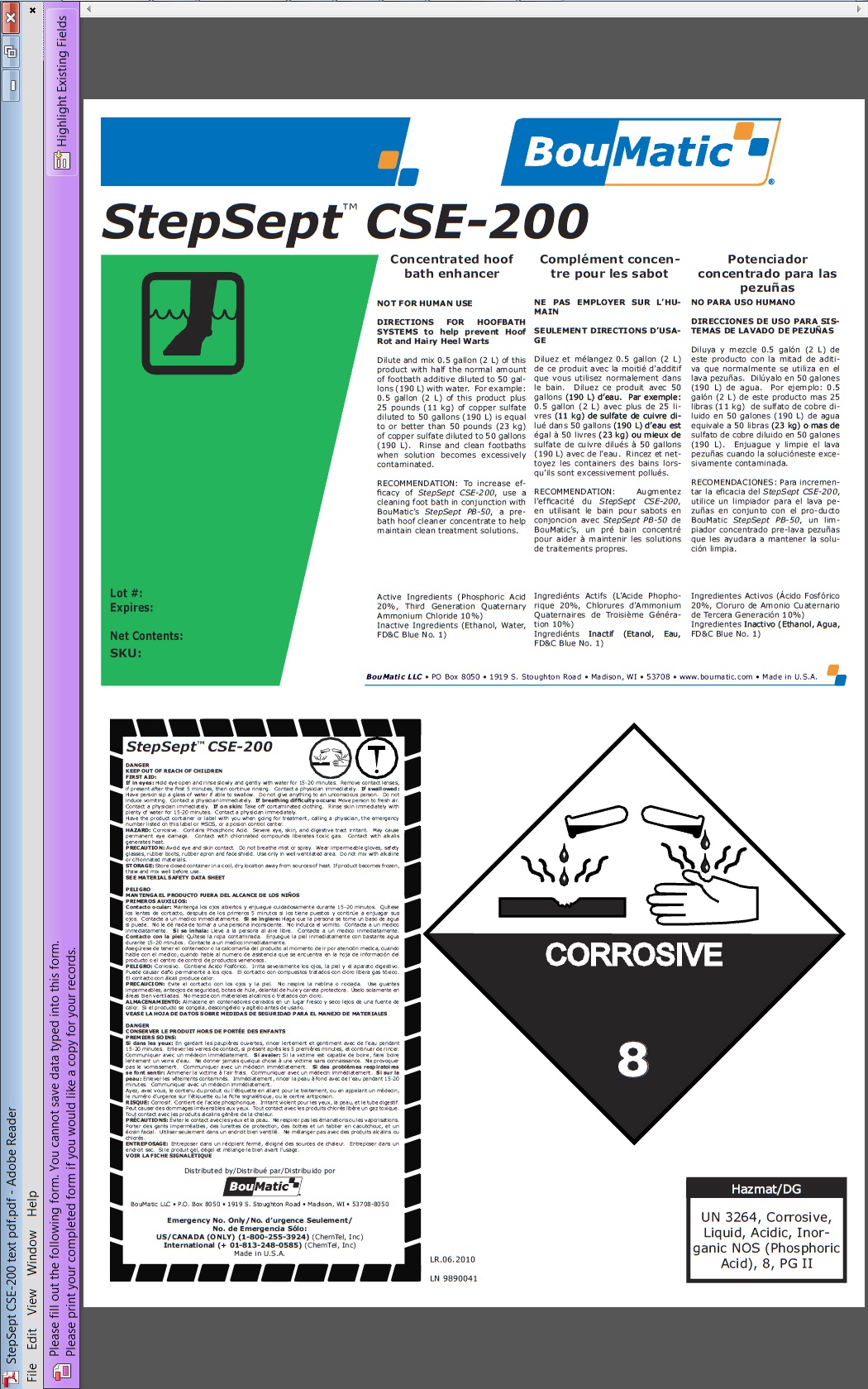 DRUG LABEL: StepSept CSE-200
NDC: 48106-1150 | Form: LIQUID
Manufacturer: BouMatic, LLC
Category: animal | Type: OTC ANIMAL DRUG LABEL
Date: 20120101

ACTIVE INGREDIENTS: PHOSPHORIC ACID 1500 mg/10 L; BENZALKONIUM CHLORIDE 400 mg/10 L; N-ALKYL ETHYLBENZYL DIMETHYL AMMONIUM CHLORIDE (C12-C14) 400 mg/10 L

StepSept CSE-200

INDICATIONS AND USAGE

Concentrated hoof bath enhancer
NOT FOR HUMAN USE
DIRECTIONS FOR HOOFBATH SYSTEMS to help prevent Hoof Rot and Hairy Heel Warts
Dilute and mix 0.5 gallon (2 L) of this product with half the normal amount of footbath additive diluted to 50 gallons (190 L) with water. For example: 0.5 gallon (2 L) of this product plus 25 pounds (11 kg) of copper sulfate diluted to 50 gallons (190 L) is equal to or better than 50 pounds (23 kg) of copper sulfate diluted to 50 gallons (190 L). Rinse and clean footbaths when solution becomes excessively contaminated.
RECOMMENDATION: To increase efficacy of StepSept CSE-200, use a cleaning foot bath in conjunction with BouMatic’s StepSept PB-50, a pre-bath hoof cleaner concentrate to help maintain clean treatment solutions.
Active Ingredients (Phosphoric Acid 20%, Third Generation Quaternary Ammonium Chloride 10%)
Inactive Ingredients (Ethanol, Water, FD(and)C Blue No. 1)

PRECAUTIONS

DANGER

KEEP OUT OF REACH OF CHILDREN

FIRST AID:

If in eyes: Hold eye open and rinse slowly and gently with water for 15-20 minutes. Remove contact lenses, if present after the first 5 minutes, then continue rinsing. Contact a physician immediately.

If swallowed: Have person sip a glass of water if able to swallow. Do not give anything to an unconscious person. Do not induce vomiting. Contact a physician immediately. If breathing difficulty occurs: Move person to fresh air. Contact a physician immediately.

If on skin: Take off contaminated clothing. Rinse skin immediately with plenty of water for 15-20 minutes. Contact a physician immediately.
Have the product container or label with you when going for treatment, calling a physician, the emergency number listed on this label or MSDS, or a poison control center.

HAZARD: Corrosive. Contains Phosphoric Acid. Severe eye, skin, and digestive tract irritant. May cause permanent eye damage. Contact with chlorinated compounds liberates toxic gas. Contact with alkalis generates heat.

PRECAUTION: Avoid eye and skin contact. Do not breathe mist or spray. Wear impermeable gloves, safety glasses, rubber boots, rubber apron and face shield. Use only in well-ventilated area. Do not mix with alkaline or chlorinated materials.

STORAGE: Store closed container in a cool, dry location away from sources of heat. If product becomes frozen, thaw and mix well before use.

SEE MATERIAL SAFETY DATA SHEET

PACKAGE LABEL

Enter section text here